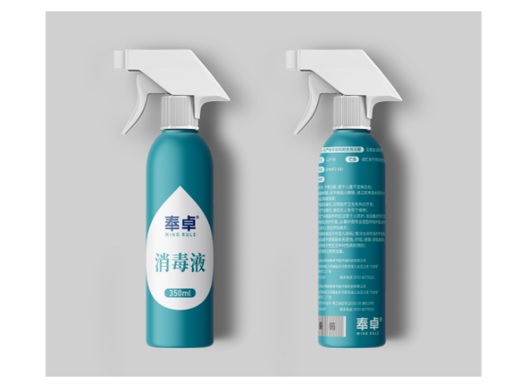 DRUG LABEL: PHYSICAL WATER		
NDC: 81910-101 | Form: LIQUID
Manufacturer: Fengzhuo Energy conservation and Environmental protection Technology
Category: otc | Type: HUMAN OTC DRUG LABEL
Date: 20210512

ACTIVE INGREDIENTS: HYPOCHLOROUS ACID 10 mg/50 mL
INACTIVE INGREDIENTS: WATER; POTASSIUM IODATE

PHYSICAL WATER

PHYSICAL WATER

Active Ingredient(s)

HYPOCHLOROUS ACID 0.01mL/50mL. Purpose: Antiseptic

Purpose

Antiseptic, PHYSICAL WATER

Use

PHYSICAL WATER to help reduce bacteria that potentially can cause disease. For use when soap and water are not available.

Warnings

For external use only.

Do not use

- in children less than 2 months of age
- on open skin wounds

When using this product keep out of eyes, ears, and mouth. In case of contact with eyes, rinse eyes thoroughly with water.
Stop use and ask a doctor if irritation or rash occurs. These may be signs of a serious condition.
Keep out of reach of children. If swallowed, get medical help or contact a Poison Control Center right away.

Stop use and ask a doctor if irritation or rash occurs. These may be signs of a serious condition.

Keep out of reach of children. If swallowed, get medical help or contact a Poison Control Center right away.

Directions

- Spray on the skin.
- Supervise children under 6 years of age when using this product to avoid swallowing.

Other information

- Store between 15-30C (59-86F)
- Avoid freezing and excessive heat above 40C (104F)

Inactive ingredients

WATER
POTASSIUM IODATE